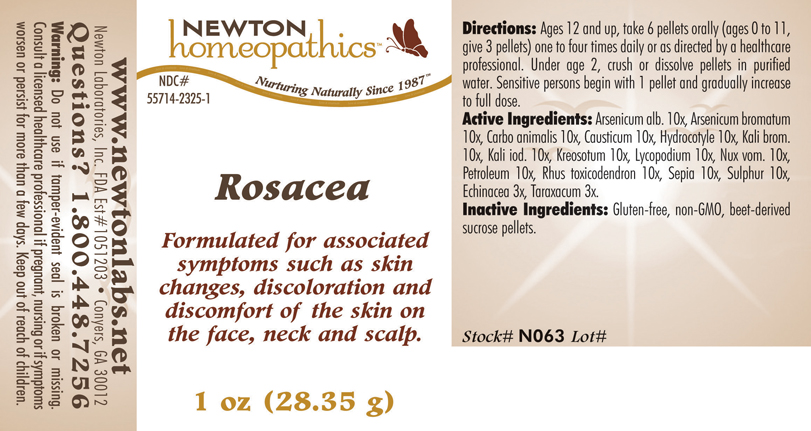 DRUG LABEL: Rosacea 
NDC: 55714-2325 | Form: PELLET
Manufacturer: Newton Laboratories, Inc.
Category: homeopathic | Type: HUMAN OTC DRUG LABEL
Date: 20110301

ACTIVE INGREDIENTS: Arsenic Trioxide 10 [hp_X]/1 g; Arsenic Tribromide 10 [hp_X]/1 g; Carbo Animalis 10 [hp_X]/1 g; Causticum 10 [hp_X]/1 g; Centella Asiatica 10 [hp_X]/1 g; Potassium Bromide 10 [hp_X]/1 g; Potassium Iodide 10 [hp_X]/1 g; Wood Creosote 10 [hp_X]/1 g; Lycopodium Clavatum Spore 10 [hp_X]/1 g; Strychnos Nux-vomica Seed 10 [hp_X]/1 g; Kerosene 10 [hp_X]/1 g; Toxicodendron Pubescens Leaf 10 [hp_X]/1 g; Sepia Officinalis Juice 10 [hp_X]/1 g; Sulfur 10 [hp_X]/1 g; Echinacea, Unspecified 3 [hp_X]/1 g; Taraxacum Officinale 3 [hp_X]/1 g
INACTIVE INGREDIENTS: Sucrose

Rosacea

INDICATIONS & USAGE SECTION

Rosacea Formulated for associated symptoms such as skin changes, discoloration and discomfort of the skin on the face, neck and scalp.

DOSAGE & ADMINISTRATION SECTION

Directions: Ages 12 and up, take 6 pellets orally (ages 0 to 11, give 3 pellets) one to four times daily or as directed by a healthcare professional. Under age 2, crush or dissolve pellets in purified water. Sensitive persons begin with 1 pellet and gradually increase to full dose.

OTC - ACTIVE INGREDIENT SECTION

Arsenicum alb. 10x, Arsenicum bromatum 10x, Carbo animalis 10x, Causticum 10x, Hydrocotyle 10x, Kali brom. 10x, Kali iod. 10x, Kreosotum 10x, Lycopodium 10x, Nux vom. 10x, Petroleum 10x, Rhus toxicodendron 10x, Sepia 10x, Sulphur 10x, Echinacea 3x, Taraxacum 3x.

OTC - PURPOSE SECTION

Formulated for associated symptoms such as skin changes, discoloration and discomfort of the skin on the face, neck and scalp.

INACTIVE INGREDIENT SECTION

Gluten-free, non-GMO, beet-derived sucrose pellets.

QUESTIONS SECTION

www.newtonlabs.net Newton Laboratories, Inc. FDA Est # 1051203 - Conyers, GA 30012
Questions? 1.800.448.7256

WARNINGS SECTION

Warning: Do not use if tamper - evident seal is broken or missing. Consult a licensed healthcare professional if pregnant, nursing or if symptoms worsen or persist for more than a few days. Keep out of reach of children

OTC - PREGNANCY OR BREAST FEEDING SECTION

Consult a licensed healthcare professional if pregnant, nursing or if symptoms worsen or persist for more than a few days.

OTC - KEEP OUT OF REACH OF CHILDREN SECTION

Keep out of reach of children.